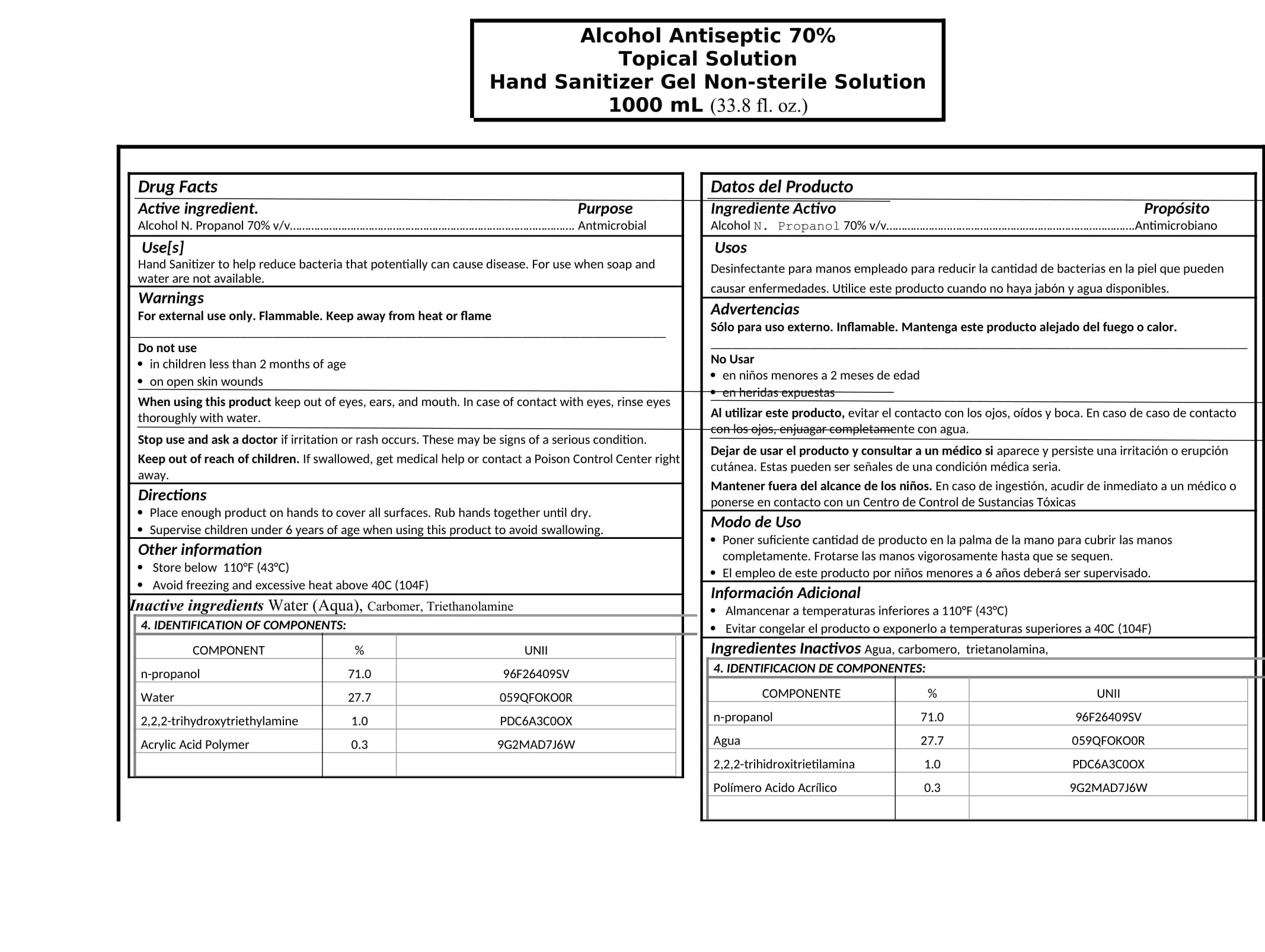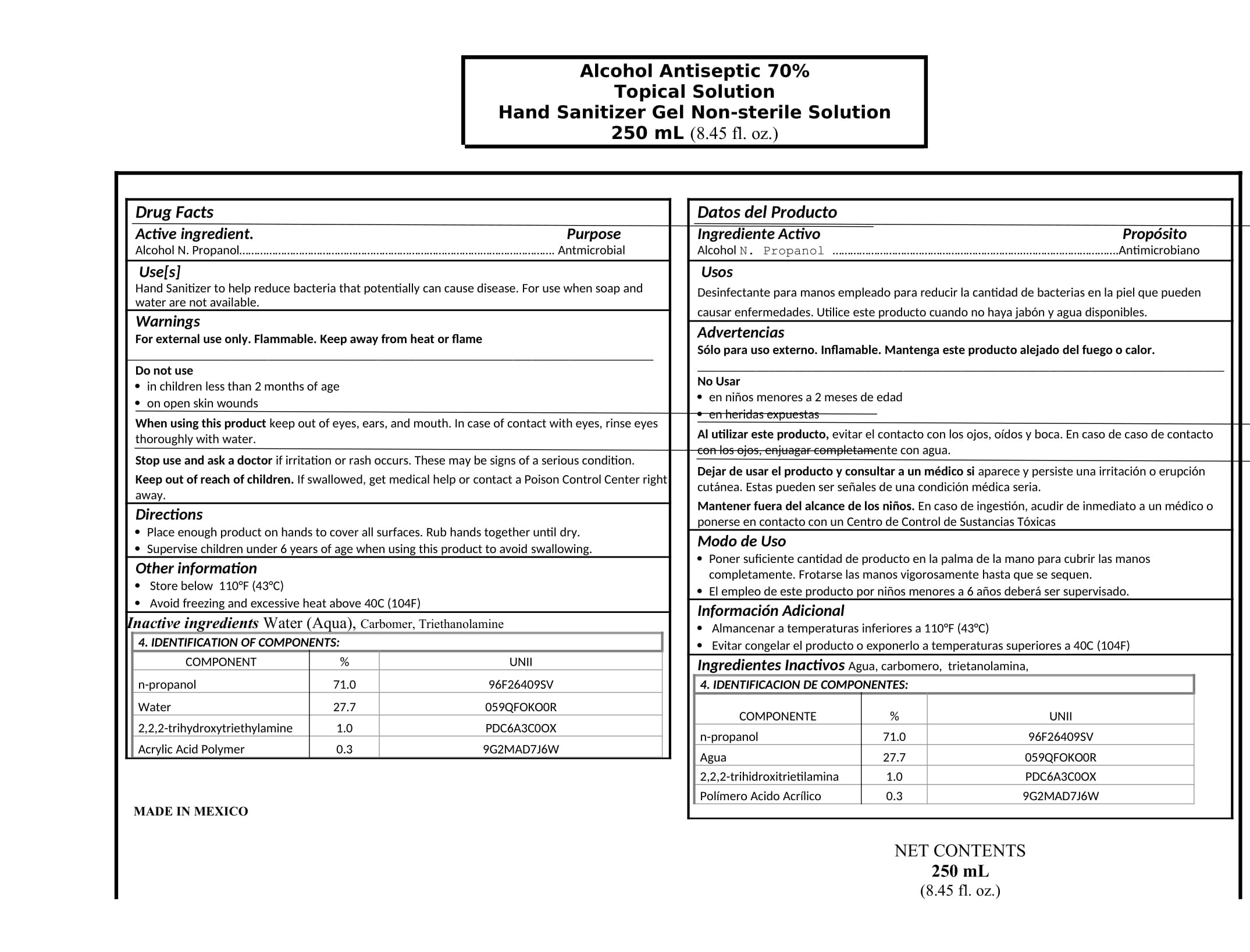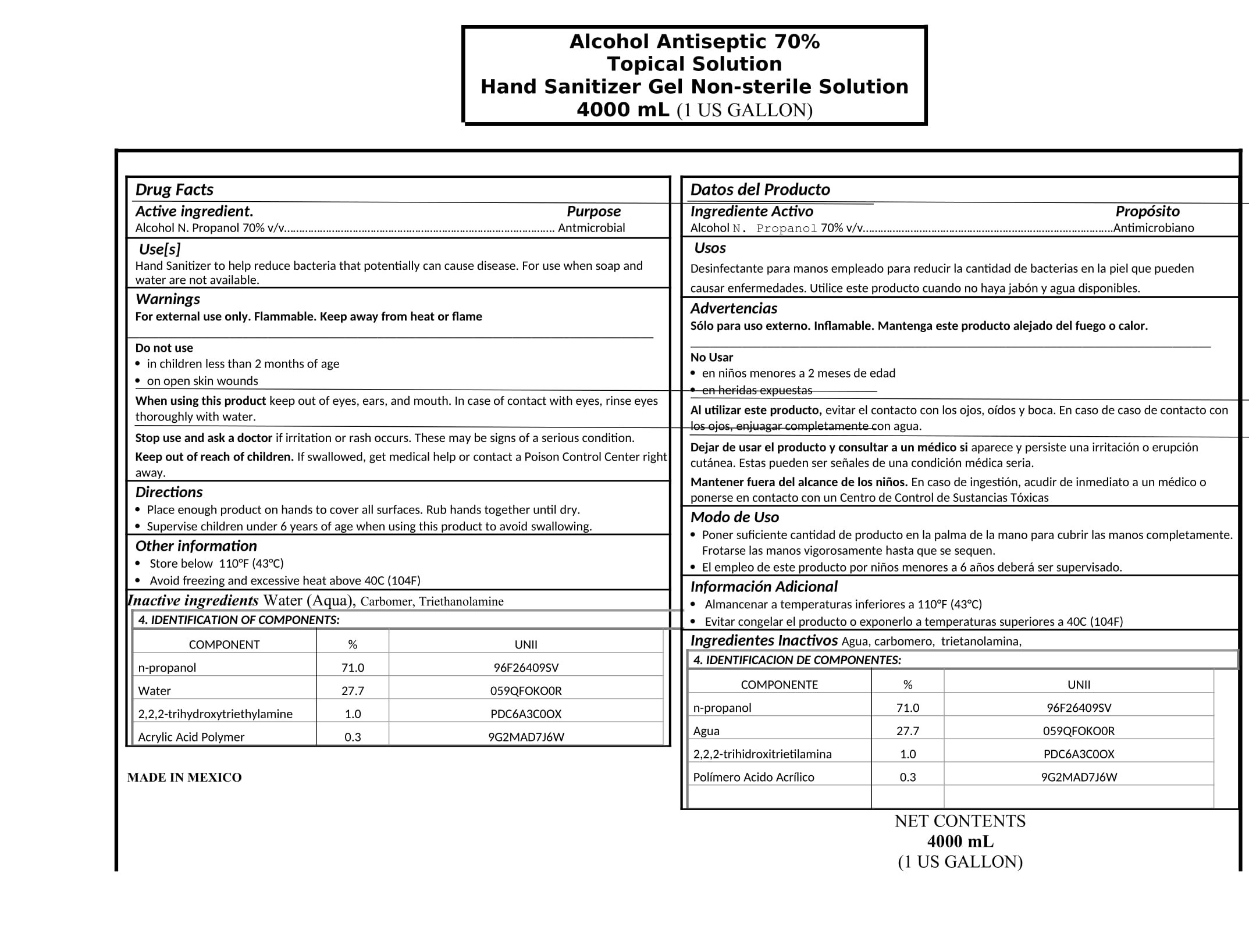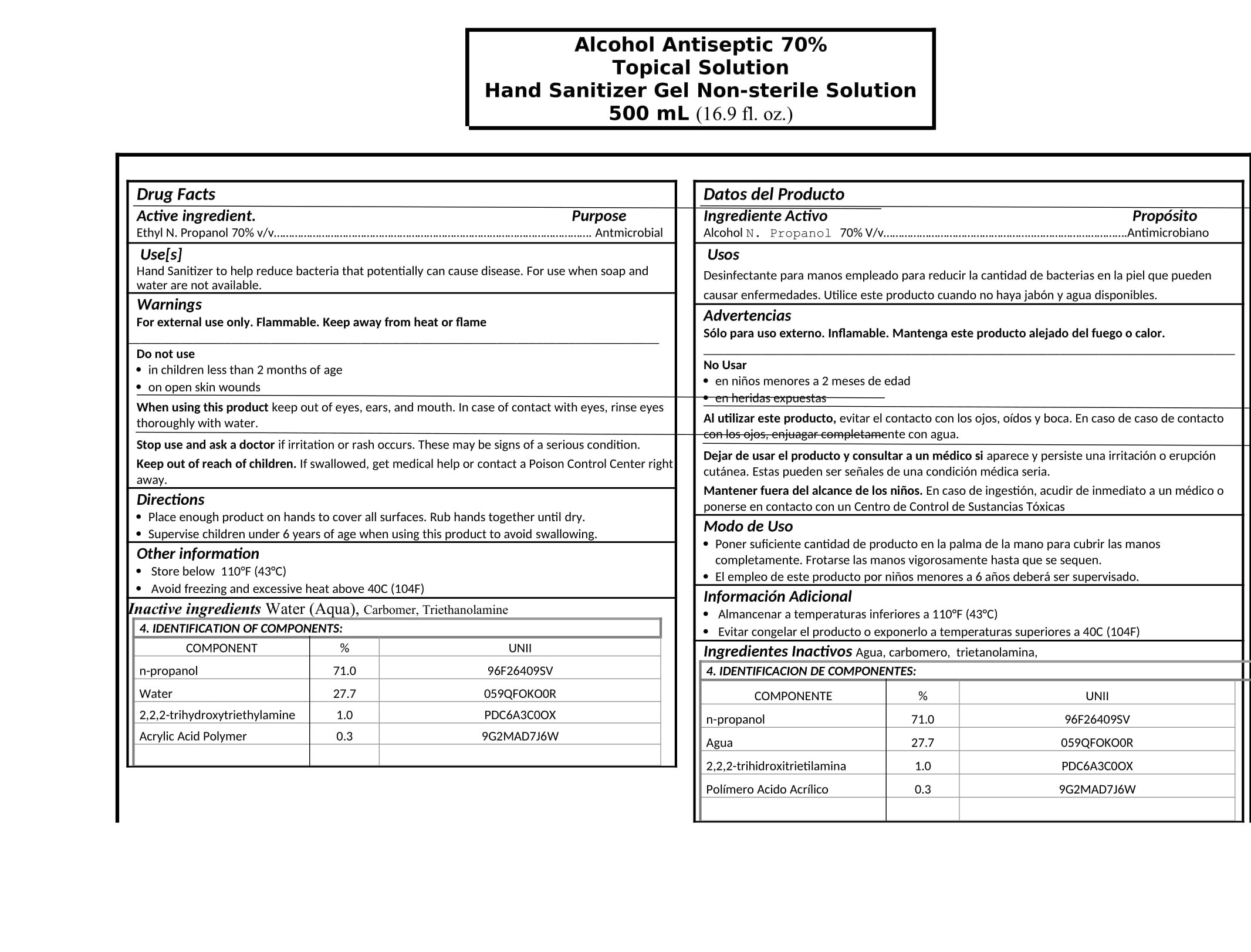 DRUG LABEL: HAND SANITIZER
NDC: 78354-0005 | Form: GEL
Manufacturer: Pomok, S.A. de C.V.
Category: otc | Type: HUMAN OTC DRUG LABEL
Date: 20200702

ACTIVE INGREDIENTS: ISOPROPYL ALCOHOL 71 mL/100 mL
INACTIVE INGREDIENTS: WATER 27.7 mL/100 mL; POLYACRYLIC ACID (250000 MW) 0.3 mL/100 mL; GLYCERIN 1 mL/100 mL

HAND SANITIZER GEL WITH PROPYL ALCOHOL

DOSAGE AND ADMINISTRATION

Directions

Place enough product on hands to cover all surfaces. Rub hands together until dry.

INACTIVE INGREDIENTS

Inactive ingredients Water (Aqua), Glycerin, Carbomer, Triethanolamine

INDICATION AND USAGE

Use[s]

Hand Sanitizer to help reduce bacteria that potentially can cause disease. For use when soap and water are not available.

Keep out of reach of children. If swallowed, get medical help or contact a Poison Control Center right away.

PURPOSE

Purpose Antmicrobial

ACTIVE INGREDIENT

Active ingredient. PROPYL ALCOHON 70% v/v…

WARNINGS AND PRECAUTIONS

Supervise children under 6 years of age when using this product to avoid swallowing.

Store below 110°F (43°C)

Avoid freezing and excessive heat above 40C (104F)

WARNINGS

For external use only. Flammable. Keep away from heat or flame